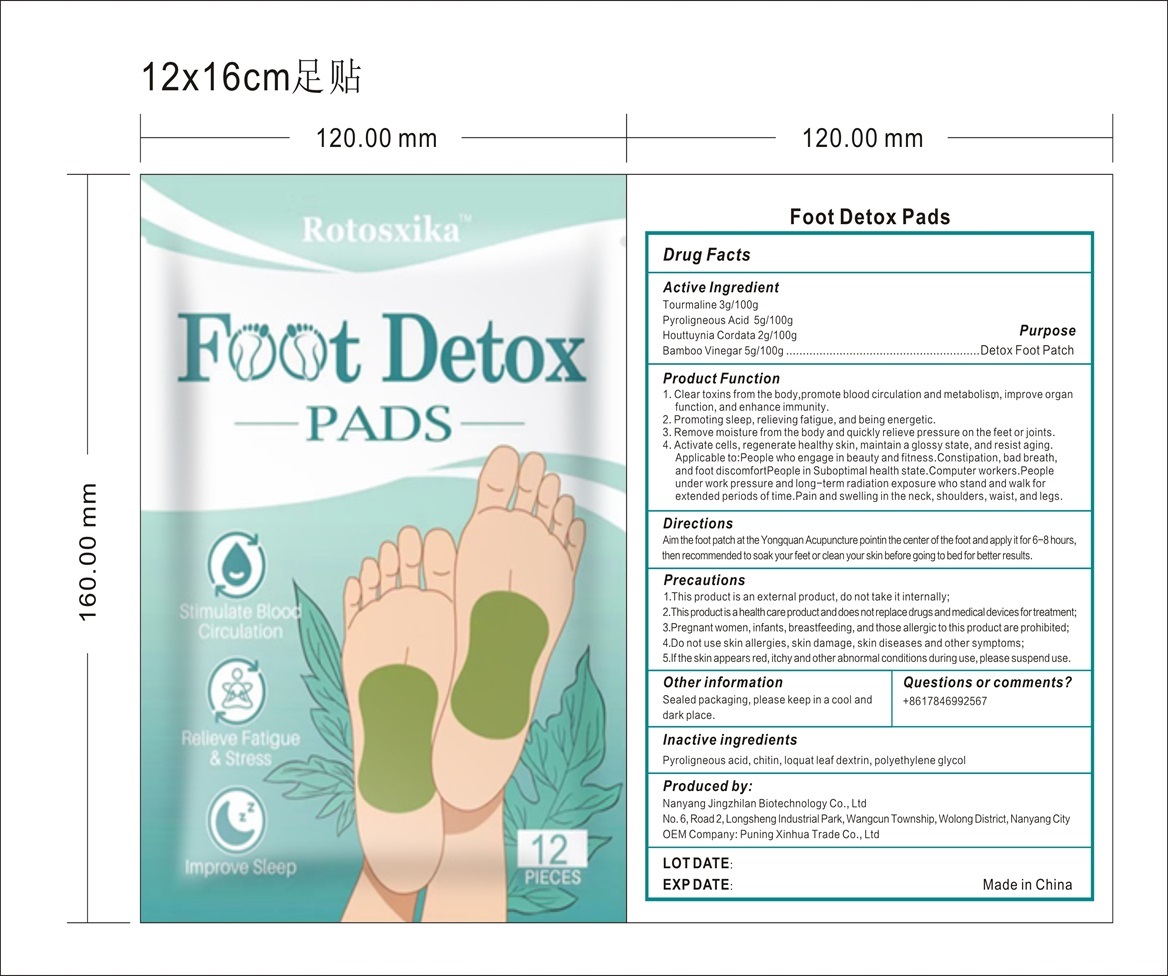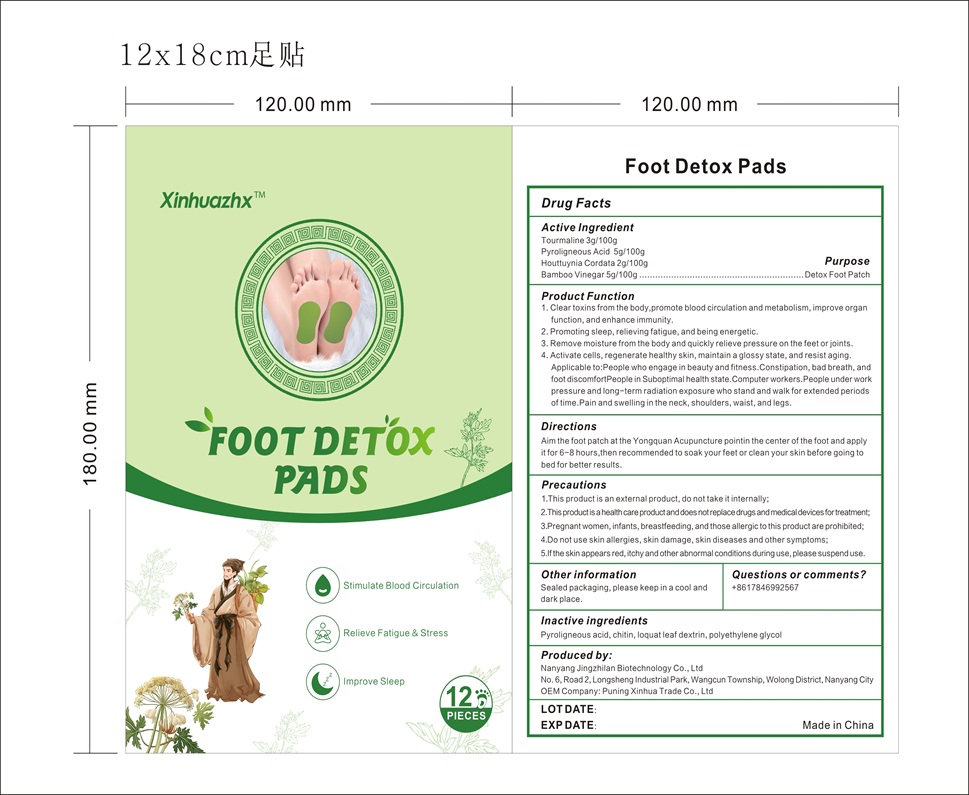 DRUG LABEL: Xinhuazhx Foot Detox Pads
NDC: 83702-011 | Form: PATCH
Manufacturer: Puning Xinhua Trade Co., Ltd.
Category: otc | Type: HUMAN OTC DRUG LABEL
Date: 20231007

ACTIVE INGREDIENTS: PYROLIGNEOUS ACID 5 g/100 g; SCHORL TOURMALINE 3 g/100 g; HOUTTUYNIA CORDATA WHOLE 2 g/100 g; BAMBUSA BAMBOS SAP 5 g/100 g
INACTIVE INGREDIENTS: CHITIN; POLYETHYLENE GLYCOL, UNSPECIFIED

Active ingredient: Bamboo vinegar 5g/100g, Tourmaline 3g/100g, Pyroligneous Acid 5g/100g, Houttuynia cordata 2g/100g

Purpose: Detox Foot Patch

INDICATIONS AND USAGE

Product Function

1. Clear toxins from the body,promote blood circulation and metabolism, improve organ function, and enhance immunity.

2. Promoting sleep, relieving fatigue, and being energetic.

3. Remove moisture from the body and quickly relieve pressure on the feet or joints.

4. Activate cells, regenerate healthy skin, maintain a glossy state, and resist aging. Applicable to:People who engage in beauty and fitness. Constipation, bad breath. and foot discomfortPeople in Suboptimal health state. Computer workers. People under work pressure and long-term radiation exposure who stand and walk for extended periods of time. Pain and swelling in the neck, shoulders, waist, and legs.

DOSAGE AND ADMINISTRATION

Directions: Aim the foot patch at the Yongquan Acupuncture pointin the center of the foot and apply it for 6-8 hours, then recommended to soak your feet or clean your skin before going to bed for better results.

WARNINGS

Precautions:

1. This product is an external product, do not take it internally;

2. This product is a health care product and does notreplace drugs and medical devices for treatment;

3. Pregnant women, infants, breastfeeding, and those allergic to this product are prohibited;

4. Do not use skin allergies, skin damage, skin diseases and other symptoms;

5. If the skin appears red, itchy and other abnormal conditions during use, please suspend use.

Questions or comments? +8617846992567

Inactive ingredients:chitin, loquat leaf dextrin, polyethylene glycol

STATEMENT OF IDENTITY

Produced by:

Nanyang Jingzhilan Biotechnology Co., Ltd

No. 6, Road 2, Longsheng Industrial Park, Wangcun Township, Wolong District, Nanyang City

OEM Company: Puning Xinhua Trade Co., Ltd

Made in China

KEEP OUT OF REACH OF CHILDREN

Same as WARNINGS SECTION

Other information: Sealed packaging, please keep in a cool and dark place.

Shelf Life: Two Years

see label